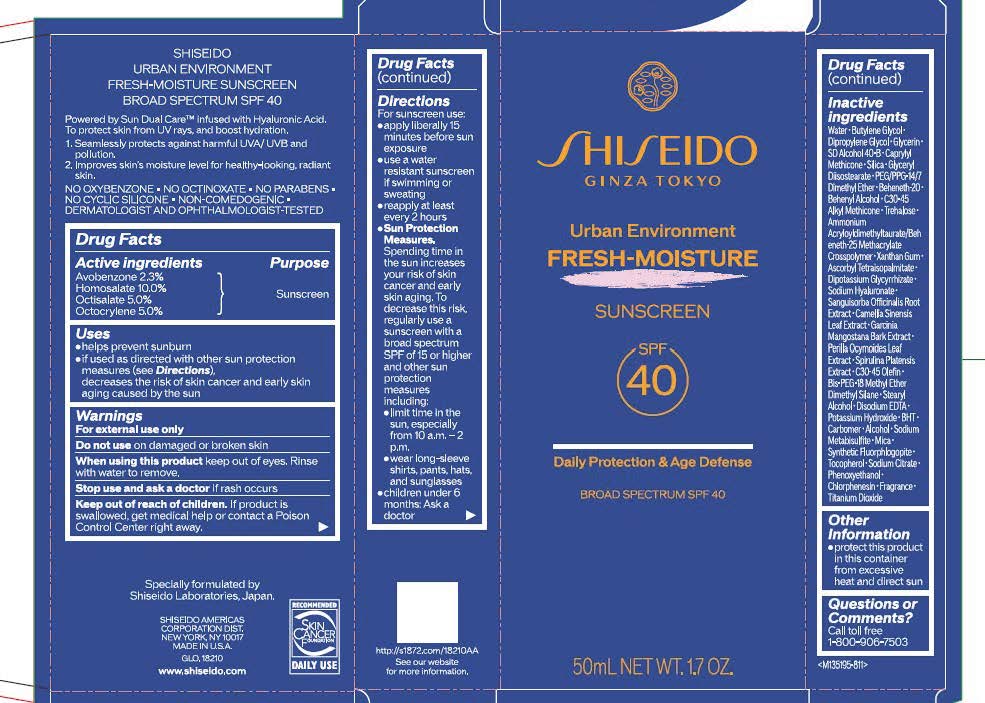 DRUG LABEL: SHISEIDO URBAN ENVIRONMENT FRESH-MOISTURE SUNSCREEN
NDC: 58411-970 | Form: CREAM
Manufacturer: Shiseido Americas Corporation
Category: otc | Type: HUMAN OTC DRUG LABEL
Date: 20260130

ACTIVE INGREDIENTS: AVOBENZONE 1.1845 g/50 mL; HOMOSALATE 5.15 g/50 mL; OCTISALATE 2.575 g/50 mL; OCTOCRYLENE 2.575 g/50 mL
INACTIVE INGREDIENTS: WATER; BUTYLENE GLYCOL; DIPROPYLENE GLYCOL; GLYCERIN; CAPRYLYL METHICONE; SILICA; GLYCERYL DIISOSTEARATE; PEG/PPG-14/7 DIMETHYL ETHER; TREHALOSE; C30-45 ALKYL METHICONE; AMMONIUM ACRYLOYLDIMETHYLTAURATE/BEHENETH-25 METHACRYLATE CROSSPOLYMER (52000 MPA.S); XANTHAN GUM; ASCORBYL TETRAISOPALMITATE; DIPOTASSIUM GLYCYRRHIZATE; SODIUM HYALURONATE; SANGUISORBA OFFICINALIS ROOT; CAMELLIA SINENSIS LEAF; GARCINIA MANGOSTANA BARK; PERILLA FRUTESCENS LEAF; SPIRULINA PLATENSIS; C30-45 OLEFIN; BIS-PEG-18 METHYL ETHER DIMETHYL SILANE; STEARYL ALCOHOL; EDETATE DISODIUM; POTASSIUM HYDROXIDE; BHT; CARBOMER; ALCOHOL; SODIUM METABISULFITE; MICA; MAGNESIUM POTASSIUM ALUMINOSILICATE FLUORIDE; TOCOPHEROL; SODIUM CITRATE; PHENOXYETHANOL; CHLORPHENESIN; TITANIUM DIOXIDE

SHISEIDO URBAN ENVIRONMENT FRESH-MOISTURE SUNSCREEN

Drug Facts

Active Ingredients | Purpose
Avobenzone 2.3% | Sunscreen
Homosalate 10% | Sunscreen
Octisalate 5.0% | Sunscreen
Octocrylene 5.0% | Sunscreen

Uses

- helps prevent sunburn
- if used as directed with other sun protection measures (see Directions), decreases the risk of skin cancer and early skin aging caused by the sun

Warnings

For external use only

Do not use ondamaged or broken skin

WHEN USING

When using this productkeep out of eyes. Rinse with water to remove.

Stop use and ask a doctorif rash occurs

Keep out of reach of children.If product is swallowed, get medical help or contact a Poison Control Center right away.

Directions

For sunscreen use:

- apply liberally 15 minutes before sun exposure
- use a water resistant sunscreen if swimming or sweating
- reapply at least every 2 hours
- Sun Protection Measures.Spending time in the sun increases your risk of skin cancer and early skin aging. To decrease this risk, regularly use a sunscreen with a broad spectrum SPF of 15 or higher and other sun protection measures including:
- limit time in the sun, especially from 10 a.m. - 2p.m.
- wear long-sleeve shirts, pant, hats, and sunglasses
- children under 6 months: Ask a doctor

INACTIVE INGREDIENT

WATER･BUTYLENE GLYCOL･DIPROPYLENE GLYCOL･GLYCERIN･SD ALCOHOL 40-B･CAPRYLYL METHICONE･SILICA･GLYCERYL DIISOSTEARATE･PEG/PPG-14/7 DIMETHYL ETHER･BEHENETH-20･BEHENYL ALCOHOL･C30-45 ALKYL METHICONE･TREHALOSE･AMMONIUM ACRYLOYLDIMETHYLTAURATE/BEHENETH-25 METHACRYLATE CROSSPOLYMER･XANTHAN GUM･ASCORBYL TETRAISOPALMITATE･DIPOTASSIUM GLYCYRRHIZATE･SODIUM HYALURONATE･SANGUISORBA OFFICINALIS ROOT EXTRACT･CAMELLIA SINENSIS LEAF EXTRACT･GARCINIA MANGOSTANA BARK EXTRACT･PERILLA OCYMOIDES LEAF EXTRACT･SPIRULINA PLATENSIS EXTRACT･C30-45 OLEFIN･BIS-PEG-18 METHYL ETHER DIMETHYL SILANE･STEARYL ALCOHOL･DISODIUM EDTA･POTASSIUM HYDROXIDE･BHT･CARBOMER･ALCOHOL･SODIUM METABISULFITE･MICA･SYNTHETIC FLUORPHLOGOPITE･TOCOPHEROL･SODIUM CITRATE･PHENOXYETHANOL･CHLORPHENESIN･FRAGRANCE･TITANIUM DIOXIDE･

Questions or Comments?

Call toll free 1-800-906-7503

Other Information

- protect this product in this container from excessive heat and direct sun.

PRINCIPLE DISPLAY PANNEL 50 mL TUBE

SHISEIDO

GINZA TOKYO

Urban Environment

FRESH-MOISTURE

SUNSCREEN

SPF 40

Daily Protection & Age Defense

BROAD SPECTRUM SPF 40

50 mL NET WT.17 OZ.